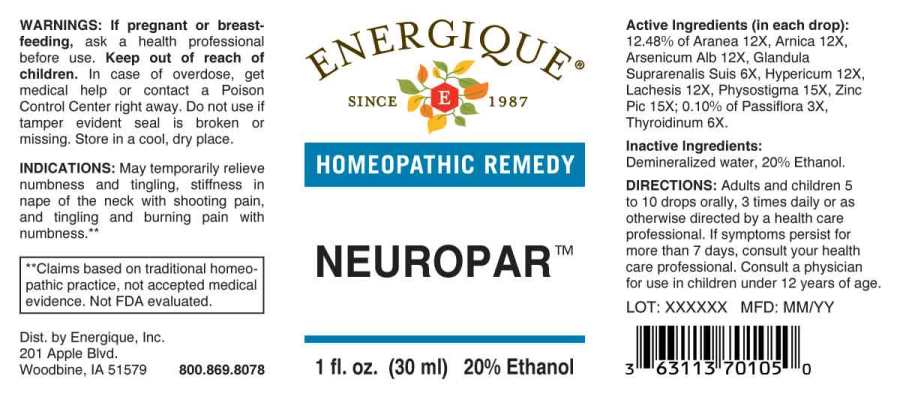 DRUG LABEL: Neuropar
NDC: 44911-0251 | Form: LIQUID
Manufacturer: Energique, Inc.
Category: homeopathic | Type: HUMAN OTC DRUG LABEL
Date: 20241029

ACTIVE INGREDIENTS: PASSIFLORA INCARNATA FLOWERING TOP 3 [hp_X]/1 mL; SUS SCROFA ADRENAL GLAND 6 [hp_X]/1 mL; THYROID, BOVINE 6 [hp_X]/1 mL; ARANEUS DIADEMATUS 12 [hp_X]/1 mL; ARNICA MONTANA WHOLE 12 [hp_X]/1 mL; ARSENIC TRIOXIDE 12 [hp_X]/1 mL; HYPERICUM PERFORATUM WHOLE 12 [hp_X]/1 mL; LACHESIS MUTA VENOM 12 [hp_X]/1 mL; PHYSOSTIGMA VENENOSUM SEED 15 [hp_X]/1 mL; ZINC PICRATE NONAHYDRATE 15 [hp_X]/1 mL
INACTIVE INGREDIENTS: WATER; ALCOHOL

DRUG FACTS:

ACTIVE INGREDIENTS:

(in each drop): 12.48% of Aranea Diadema 12X, Arnica Montana 12X, Arsenicum Album 12X, Glandula Suprarenalis Suis 6X, Hypericum Perforatum 12X, Lachesis Mutus 12X, Physostigma Venenosum 15X, Zincum Picricum 15X; 0.10% of Passiflora Incarnata 3X, Thyroidinum (Bovine) 6X.

INDICATIONS:

May temporarily relieve numbness and tingling, stiffness in nape of the neck with shooting pain, and tingling and burning pain with numbness.**

**Claims based on traditional homeopathic practice, not accepted medical evidence. Not FDA evaluated.

WARNINGS:

If pregnant or breast-feeding, ask a health professional before use.

Keep out of reach of children. In case of overdose, get medical help or contact a Poison Control Center right away.

Do not use if tamper evident seal is broken or missing. Store in a cool, dry place.

Keep out of reach of children. In case of overdose, get medical help or contact a Poison Control Center right away.

DIRECTIONS:

Adults and children 5 to 10 drops orally, 3 times daily or as otherwise directed by a health care professional. If symptoms persist for more than 7 days, consult your health care professional. Consult a physician for use in children under 12 years of age.

INDICATIONS:

May temporarily relieve numbness and tingling, stiffness in nape of the neck with shooting pain, and tingling and burning pain with numbness.**

**Claims based on traditional homeopathic practice, not accepted medical evidence. Not FDA evaluated.

INACTIVE INGREDIENTS:

Demineralized water, 20% Ethanol.

QUESTIONS:

Dist. by Energique, Inc.

201 Apple Blvd.

Woodbine, IA 51579 800.869.8078

PACKAGE LABEL DISPLAY:

ENERGIQUE
SINCE 1987
HOMEOPATHIC REMEDY
NEUROPAR
1 fl. oz. (30 ml)